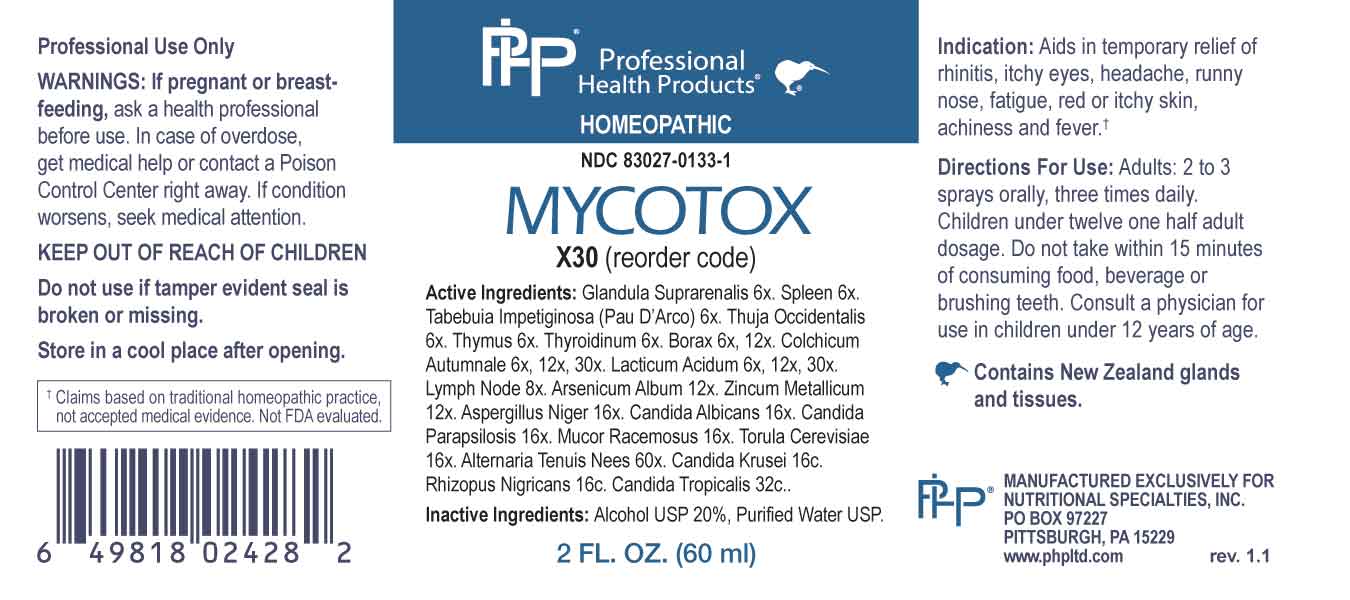 DRUG LABEL: Mycotox
NDC: 83027-0133 | Form: SPRAY
Manufacturer: Nutritional Specialties, Inc.
Category: homeopathic | Type: HUMAN OTC DRUG LABEL
Date: 20240925

ACTIVE INGREDIENTS: BOS TAURUS ADRENAL GLAND 6 [hp_X]/1 mL; BOS TAURUS SPLEEN 6 [hp_X]/1 mL; HANDROANTHUS IMPETIGINOSUS BARK 6 [hp_X]/1 mL; THUJA OCCIDENTALIS LEAFY TWIG 6 [hp_X]/1 mL; LAMB 6 [hp_X]/1 mL; THYROID, BOVINE 6 [hp_X]/1 mL; SODIUM BORATE 6 [hp_X]/1 mL; COLCHICUM AUTUMNALE BULB 6 [hp_X]/1 mL; LACTIC ACID, DL- 6 [hp_X]/1 mL; SUS SCROFA LYMPH 8 [hp_X]/1 mL; ARSENIC TRIOXIDE 12 [hp_X]/1 mL; ZINC 12 [hp_X]/1 mL; ASPERGILLUS NIGER VAR. NIGER 16 [hp_X]/1 mL; CANDIDA ALBICANS 16 [hp_X]/1 mL; CANDIDA PARAPSILOSIS 16 [hp_X]/1 mL; MUCOR RACEMOSUS 16 [hp_X]/1 mL; SACCHAROMYCES CEREVISIAE 16 [hp_X]/1 mL; ALTERNARIA ALTERNATA 60 [hp_X]/1 mL; ISSATCHENKIA ORIENTALIS WHOLE 16 [hp_C]/1 mL; RHIZOPUS STOLONIFER 16 [hp_C]/1 mL; CANDIDA TROPICALIS 32 [hp_C]/1 mL
INACTIVE INGREDIENTS: WATER; ALCOHOL

DRUG FACTS:

ACTIVE INGREDIENTS:

Glandula Suprarenalis 6X, Spleen 6X, Tabebuia Impetiginosa (Pau D’Arco) 6X, Thuja Occidentalis 6X, Thymus 6X, Thyroidinum 6X, Borax 6X, 12X, Colchicum Autumnale 6X, 12X, 30X, Lacticum Acidum 6X, 12X, 30X, Lymph Node 8X, Arsenicum Album 12X, Zincum Metallicum 12X, Aspergillus Niger 16X, Candida Albicans 16X, Candida Parapsilosis 16X, Mucor Racemosus 16X, Torula Cerevisiae 16X, Alternaria Tenuis Nees 60X, Candida Krusei 16C, Rhizopus Nigricans 16C, Candida Tropicalis 32C.

PURPOSE:

Aids in temporary relief of rhinitis, itchy eyes, headache, runny nose, fatigue, red or itchy skin, achiness and fever.†

†Claims based on traditional homeopathic practice, not accepted medical evidence. Not FDA evaluated.

WARNINGS:

Professional Use Only

If pregnant or breast-feeding, ask a health professional before use.

In case of overdose, get medical help or contact a Poison Control Center right away.

If condition worsens, seek medical attention.

KEEP OUT OF REACH OF CHILDREN

Do not use if tamper evident seal is broken or missing.

Store in a cool place after opening

KEEP OUT OF REACH OF CHILDREN:

In case of overdose, get medical help or contact a Poison Control Center right away.

DIRECTIONS:

Adults: 2 to 3 sprays orally, three times daily. Children under twelve one half adult dosage. Do not take within 15 minutes of consuming food, beverage or brushing teeth. Consult a physician for use in children under 12 years of age.

INDICATIONS:

Aids in temporary relief of rhinitis, itchy eyes, headache, runny nose, fatigue, red or itchy skin, achiness and fever.†

†Claims based on traditional homeopathic practice, not accepted medical evidence. Not FDA evaluated.

INACTIVE INGREDIENTS:

Alcohol USP 20%, Purified Water USP.

QUESTIONS:

MANUFACTURED EXCLUSIVELY FOR

NUTRITIONAL SPECIALTIES, INC.

PO BOX 97227

PITTSBURG, PA 15229

www.phpltd.com

PACKAGE LABEL DISPLAY:

Professional

Health Products

HOMEOPATHIC

NDC 83027-0133-1

MYCOTOX

2 FL. OZ (60 ml)